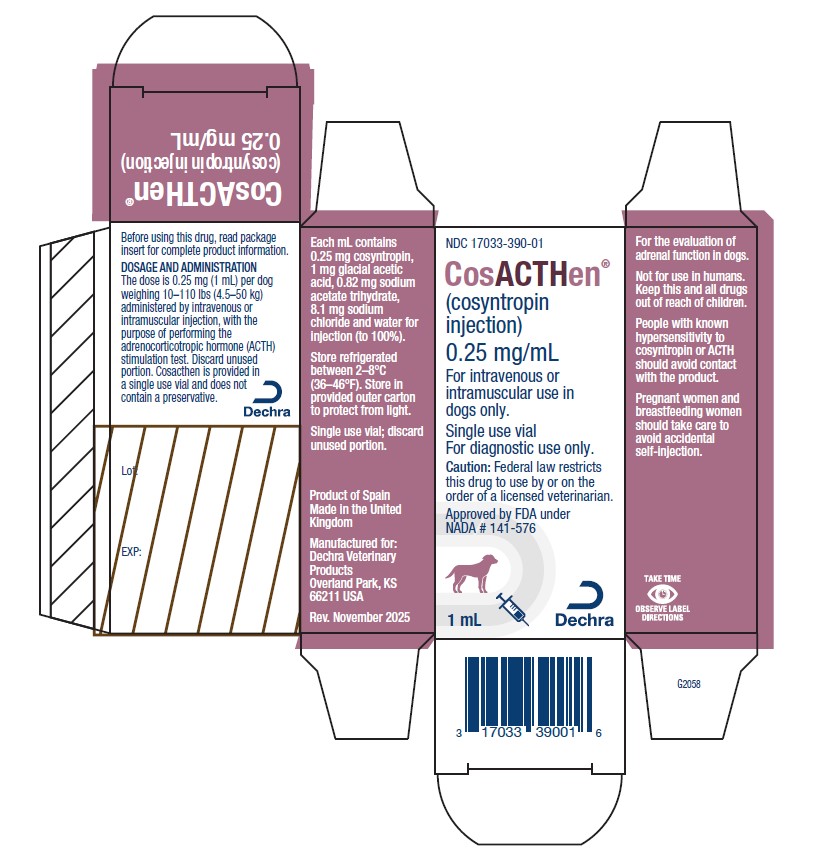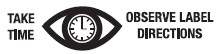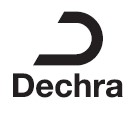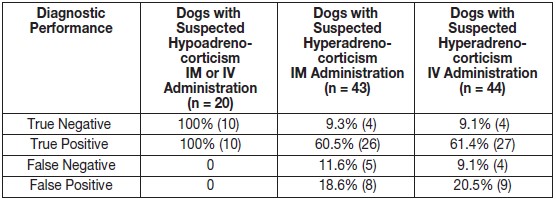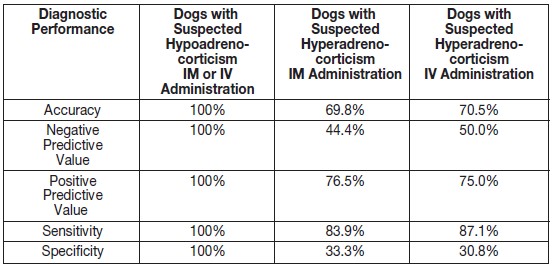 DRUG LABEL: CosACTHen
NDC: 17033-390 | Form: INJECTION
Manufacturer: Dechra Veterinary Products, LLC
Category: animal | Type: PRESCRIPTION ANIMAL DRUG LABEL
Date: 20260114

ACTIVE INGREDIENTS: COSYNTROPIN 0.25 mg/1 mL

CosACTHen®
(cosyntropin injection)

For intravenous or intramuscular use in dogs only.

CAUTION:

Federal law restricts this drug to use by or on the order of a licensed veterinarian.

DESCRIPTION

Cosyntropin consists of the first 24 amino acids in naturally occurring adrenocorticotropic hormone (ACTH). The sequence of amino acids in cosyntropin is as follows:

Ser-Tyr-Ser-Met-Glu-His-Phe-Arg-Trp-Gly-Lys-Pro-Val-Gly-Lys-Lys-Arg-Arg-Pro-Val- Lys-Val-Tyr-Pro

Molecular formula: C136 H210N40O31S

Cosacthen® (cosyntropin injection) is a clear, aqueous solution. Each milliliter contains 0.25 mg cosyntropin, 1 mg glacial acetic acid, 0.82 mg sodium acetate trihydrate, 8.1 mg sodium chloride and water for injection (to 100%).

INDICATION

For the evaluation of adrenal function in dogs.

DOSAGE AND ADMINISTRATION

The dose is 0.25 mg (1 mL) per dog weighing 10–110 lbs (4.5–50 kg), administered by intravenous or intramuscular injection, with the purpose of performing the adrenocorticotropic hormone (ACTH) stimulation test. Discard unused portion. Cosacthen is provided in a single use vial and does not contain a preservative.

Collect the first blood sample to measure the baseline cortisol concentration immediately prior to administering Cosacthen. Collect the second blood sample 1 hour after administration of Cosacthen to measure the dog’s cortisol concentration in response to Cosacthen.

CONTRAINDICATIONS

Do not use Cosacthen in dogs that have previously had a hypersensitivity reaction to cosyntropin.

WARNINGS USER SAFETY WARNINGS

Not for use in humans. Keep this and all drugs out of reach of children.

People with known hypersensitivity to cosyntropin or ACTH should avoid contact with the product.

Pregnant women and breastfeeding women should take care to avoid accidental self-injection.

If any anaphylactic or allergic symptoms (skin reactions, dizziness, nausea, vomiting, urticaria, pruritus, flushing, malaise, dyspnea, angioneurotic edema) develop following exposure to Cosacthen, medical advice must be sought immediately. In case of accidental self-injection, seek medical advice immediately and show the package insert or label to the physician.

If skin contact occurs, wash affected area with soap and water.

PRECAUTIONS

The safe use of Cosacthen has not been evaluated in breeding, pregnant, or lactating dogs.

ADVERSE REACTIONS

In the field study using a non-final formulation cosyntropin injection, which included 119 dogs with suspected hypoadrenocorticism or hyperadrenocorticism, two dogs vomited within 8 hours after cosyntropin injection administration, and one dog developed a hematoma at the injection site after IV administration. Clinical pathology abnormalities were consistent with pre-existing hypoadrenocorticism and hyperadrenocorticism.

Foreign Market Experience: The following adverse events were reported voluntarily during post-approval use of Cosacthen in dogs in foreign markets: lethargy, anxiety, muscle tremor/weakness, abdominal pain, anorexia, diarrhea, injection site pain/bruising, lameness, and hypersensitivity reactions.

CONTACT INFORMATION

To report suspected adverse drug experiences, or for technical assistance, contact Dechra Veterinary Products at (866) 933-2472.

For additional information about reporting adverse drug experiences for animal drugs, contact FDA at 1-888-FDA-VETS or online at http://www.fda.gov/reportanimalae

CLINICAL PHARMACOLOGY

Cosyntropin, like ACTH, binds specific receptors in the plasma membrane of adrenal cortical cells in the zona fasciculata. The hormone-receptor complex activates adenylate cyclase, which stimulates the production of cyclic AMP. This leads to the conversion of cholesterol to pregnenolone, and thus to the production of various glucocorticoids via their respective synthetic pathways.

EFFECTIVENESS

Cosacthen was evaluated in a laboratory effectiveness study in 16 healthy, 9- to 56-month-old beagle dogs. Eight dogs were administered Cosacthen intramuscularly (IM) at a dose of 0.005 mg/kg. Eight control dogs were administered saline. All dogs in the Cosacthen group had a positive response (defined as a change from a pre-dose serum cortisol concentration of 0.5–6.5 μg/dL to a post-dose serum cortisol concentration greater than 6.5 μg/dL) at 30, 60, and 90 minutes after administration. No dogs in the control group had a positive response.

The mean serum cortisol concentration 60 minutes after Cosacthen or saline administration was 12.9 μg/dL (range 10.6–14.6 μg/dL) and 2.3 μg/dL (range 0.8–3.4 μg/dL), respectively.

A non-final formulation of cosyntropin injection was evaluated in a randomized, unmasked multi-site field study to evaluate effectiveness, diagnostic performance, and safety. One hundred nineteen dogs suspected of having hypoadrenocorticism (21) or hyperadrenocorticism (98) were randomized to two treatment groups and administered cosyntropin injection at 0.25 mg/dog once by IM or IV injection. Blood samples were collected prior to dosing to assess baseline serum cortisol concentrations and again 60 minutes after cosyntropin injection administration.

Diagnostic performance was evaluated in 107 dogs and safety was evaluated in 119 dogs. The true and false negative and positive results are summarized in Table 1. The accuracy, negative and positive predictive values, sensitivity, and specificity results are summarized in Table 2.

Table 1. True and False Negative and Positive Results for Non-Final Formulation Cosyntropin Injection

Table 2. Accuracy, Negative and Positive Predictive Value, Sensitivity, and Specificity of Non-Final Formulation Cosyntropin Injection

Two dogs vomited within 8 hours after cosyntropin injection administration. One dog developed a hematoma following IV administration of cosyntropin injection.

TARGET ANIMAL SAFETY

A non-final formulation of cosyntropin injection was administered to 32 healthy, 5- to 6-month-old beagle dogs as 3 weekly IV or IM injections. Twenty IV-dosed dogs were administered multiples of 0X (4), 1X (4), 3X (4), or 5X (8) and 12 IM-dosed dogs were administered multiples of 0X (4), 1X (4), or 2X (4) the maximum exposure dose of 0.056 mg/kg. Control dogs were administered saline.

All dogs completed the study. Clinical signs related to cosyntropin injection administration included transient salivation during and/or immediately after dosing in six of eight dogs in the 5X, IV-dosed group, during the third dose. Of these six dogs, one male and one female were also observed salivating during the second IV administration of cosyntropin injection. One of the 5X, IV-dosed dogs had a hypersensitivity reaction to its third injection. The reaction started within 3 minutes of dosing and included: transient salivation, injected mucous membranes, inguinal erythema, facial edema, and tachycardia. After 1 hour, the facial edema had improved; the other signs persisted for approximately 150 minutes. The dog recovered without medical intervention. One of four 1X, IV-dosed dogs and three of eight 5X, IV-dosed dogs vomited once within an hour of dosing.

STORAGE INFORMATION

Store refrigerated between 2–8°C (36–46°F). Store in provided outer carton to protect from light.

Single use vial; discard unused portion.

HOW SUPPLIED

Cosacthen® (cosyntropin injection) is supplied in a clear glass vial with 1 mL cosyntropin (0.25 mg/mL).

NDC 17033-390-01

Approved by FDA under NADA # 141-576

Manufactured for:
Dechra Veterinary Products
7015 College Boulevard, Suite 525
Overland Park, KS 66211 USA

Cosacthen is a registered trademark of Dechra Limited.

Rev. November 2025

F1585

PRINCIPAL DISPLAY PANEL - 1 mL Vial

NDC 17033-390-01

CosACTHen®
(cosyntropin injection)

0.25 mg/mL

For intravenous or intramuscular use in dogs only.

Single use vial
For diagnostic use only.

Caution: Federal law restricts this drug to use by or on the order of a licensed veterinarian.

Approved by FDA under NADA # 141-576

1 mL

Dechra